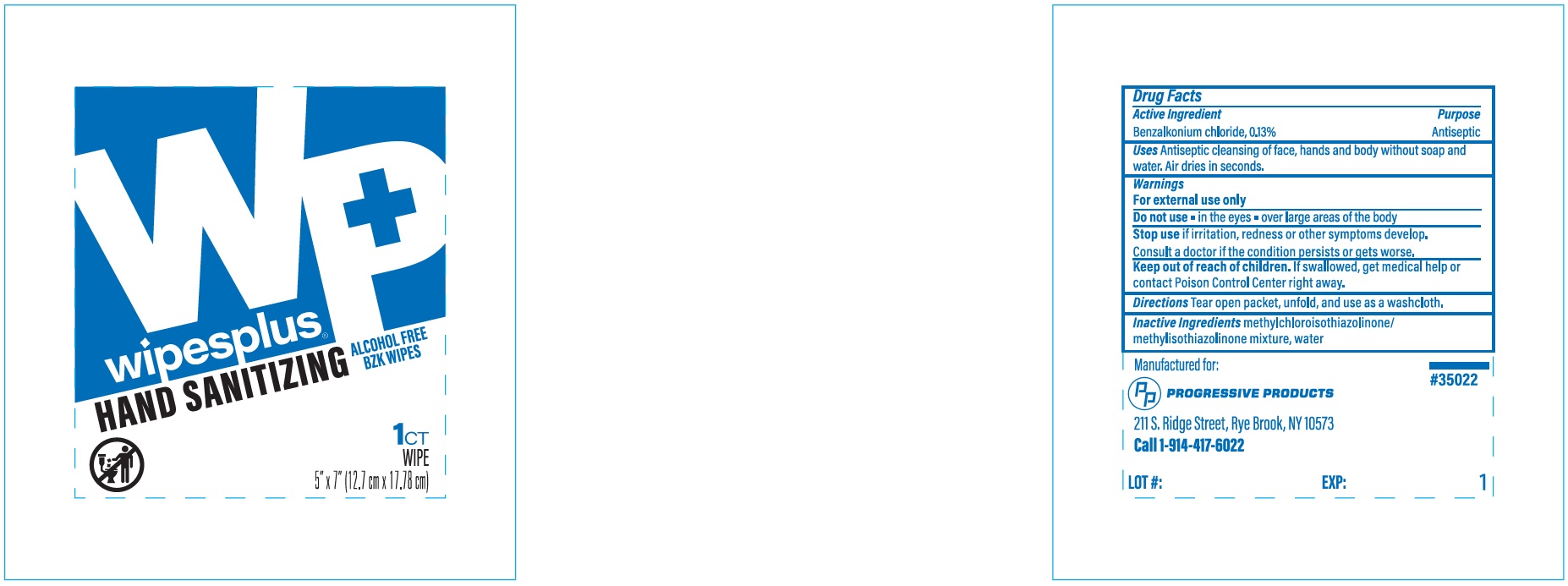 DRUG LABEL: Wipesplus Hand Sanitizing Alcohol Free BZK Wipes
NDC: 67151-333 | Form: CLOTH
Manufacturer: Progressive Products, LLC
Category: otc | Type: HUMAN OTC DRUG LABEL
Date: 20221014

ACTIVE INGREDIENTS: BENZALKONIUM CHLORIDE 0.0013 mg/100 mg
INACTIVE INGREDIENTS: METHYLCHLOROISOTHIAZOLINONE; WATER

Drug Facts

Active Ingredient

Benzalkonium Chloride, 0.13%

Purpose

Antiseptic

Uses

Antiseptic cleansing of face, hands and body without soap and water. Air dries in seconds.

Warnings

For external use only

Do not use

- in the eyes
- over large areas of the body

Stop use

if irritation, redness or other symptoms develop. Consult a doctor if the condition persists or gets worse.

Keep out of reach of children.

If swallowed, get medical help or contact Poison Control Center right away.

Directions

Tear open packet, unfold, and use as a washcloth.

Inactive Ingredients

methylchloroisothiazolinone/methylisothiazolinone mixture, water

Principal Display Panel

wipesplus

HAND SANITIZING

ALCOHOL FREE BZK WIPES

1 CT WIPE